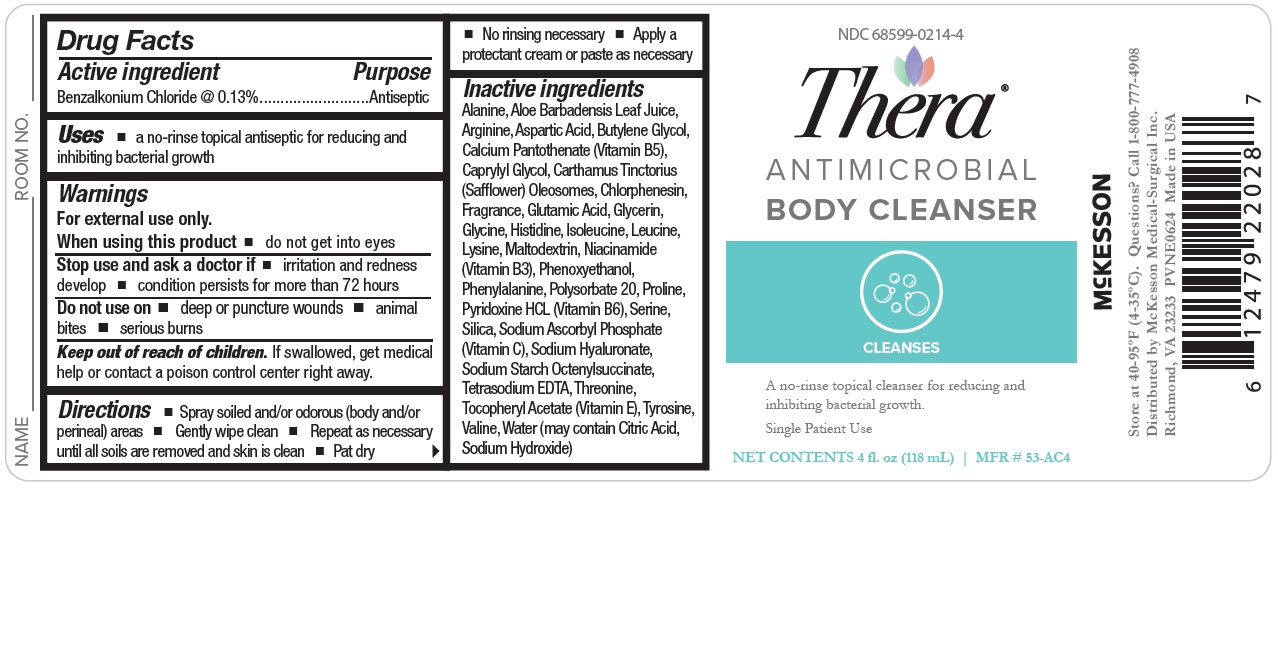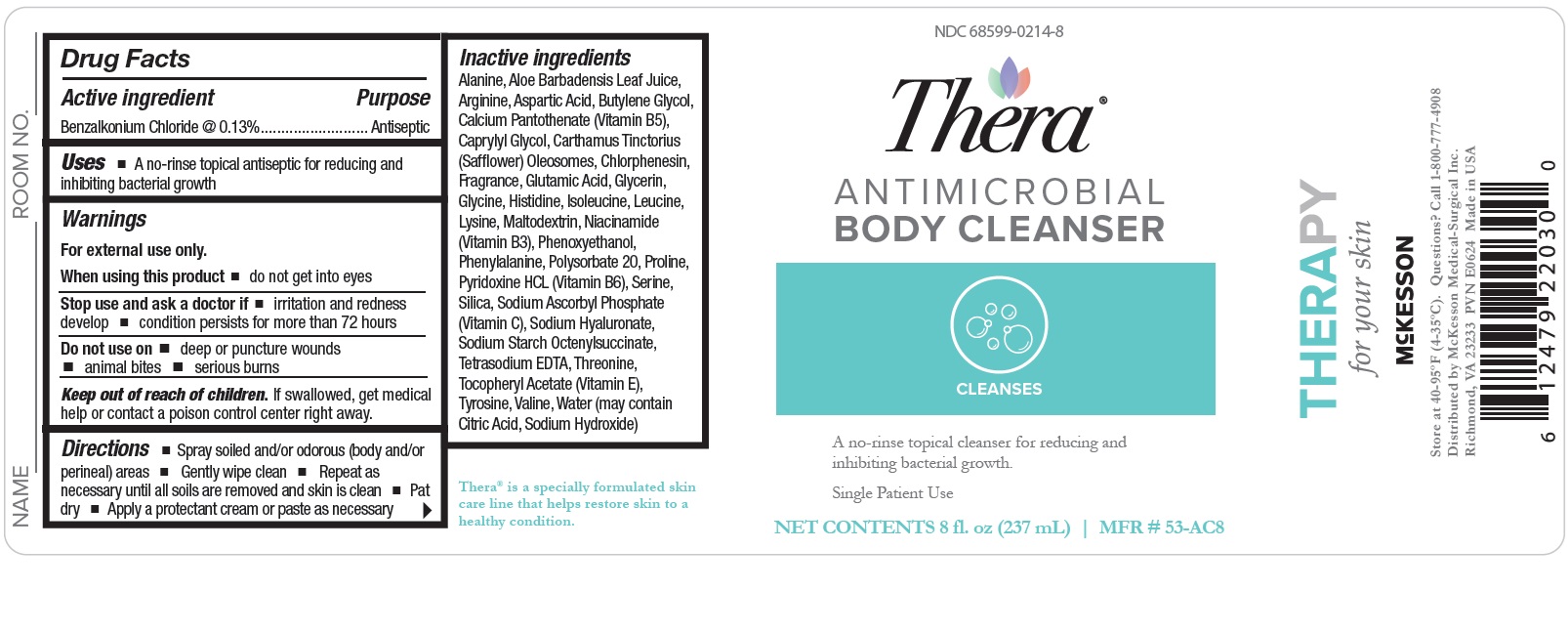 DRUG LABEL: Antimicrobial
NDC: 68599-0214 | Form: LIQUID
Manufacturer: McKesson
Category: otc | Type: HUMAN OTC DRUG LABEL
Date: 20240617

ACTIVE INGREDIENTS: BENZALKONIUM CHLORIDE 1.3 ug/1 mg
INACTIVE INGREDIENTS: WATER; PROLINE; VALINE; LEUCINE; NIACINAMIDE; .ALPHA.-TOCOPHEROL ACETATE; LYSINE; GLYCERIN; POLYSORBATE 20; PHENYLALANINE; ARGININE; CAPRYLYL GLYCOL; CHLORPHENESIN; SODIUM ASCORBYL PHOSPHATE; OCTENYLSUCCINIC ACID; THREONINE; GLYCINE; EDETATE SODIUM; HISTIDINE; ISOLEUCINE; CARTHAMUS TINCTORIUS (SAFFLOWER) OLEOSOMES; CALCIUM PANTOTHENATE; MALTODEXTRIN; PYRIDOXINE HYDROCHLORIDE; ASPARTIC ACID; GLUTAMIC ACID; ALANINE; TYROSINE; SERINE; BUTYLENE GLYCOL; PHENOXYETHANOL; SILICON DIOXIDE; ALOE VERA LEAF; HYALURONATE SODIUM

Antimicrobial Body Cleanser

Drug Facts

Active ingredient
Benzalkonium Chloride 0.13%

Purpose
Antiseptic

Uses
a no-rinse topical antiseptic for reducing and inhibiting bacterial growth.

Warnings
For external use only.
When using this product

- do not get into eyes

Do not use on

- deep or puncture wounds
- animal bites
- serious burns

Stop use and ask a doctor if

- irritation and redness develop
- condition persists for more than 72 hours

Keep out of reach of children.
If swallowed, get medical help or contact a poison control center right away.

Directions

- Spray soiled and/or odorous (body and/or perineal) areas
- Gently wipe clean
- Repeat as necessary until all soils are removed and skin is clean
- Pat dry
- No rinsing necessary
- Apply a protectant cream or paste as necessary

OTHER SAFETY INFORMATION

Store at 40-95ºF (4-35ºC)

Inactive ingredients
Alanine, Aloe Barbadensis Leaf Juice,
Arginine, Aspartic Acid, Butylene Glycol,
Calcium Pantothenate (Vitamin B5),
Caprylyl Glycol, Carthamus Tinctorius
(Safflower) Oleosomes, Chlorphenesin,
Fragrance, Glutamic Acid, Glycerin,
Glycine, Histidine, Isoleucine, Leucine,
Lysine, Maltodextrin, Niacinamide
(Vitamin B3), Phenoxyethanol,
Phenylalanine, Polysorbate 20, Proline,
Pyridoxine HCL (Vitamin B6), Serine,
Silica, Sodium Ascorbyl Phosphate
(Vitamin C), Sodium Hyaluronate,
Sodium Starch Octenylsuccinate,
Tetrasodium EDTA, Threonine,
Tocopheryl Acetate (Vitamin E), Tyrosine,
Valine, Water (may contain Citric Acid,
Sodium Hydroxide)

Questions?
Call 1-800-777-4908

PACKAGE LABEL

NDC 68599-0214-4
McKesson
Thera
ANTIMICROBIAL BODY CLEANSER
A no-rinse topical cleanser for reducing and inhibiting bacterial growth.
Single Patient Use
NET CONTENTS 4 fl. oz (118 mL)
MFR # 53-AC4

PACKAGE LABEL

NDC 68599-0214-8
McKesson
Thera
ANTIMICROBIAL BODY CLEANSER
A no-rinse topical cleanser for reducing and inhibiting bacterial growth.
Single Patient Use
NET CONTENTS 8 fl. oz (237 mL)
MFR # 53-AC8